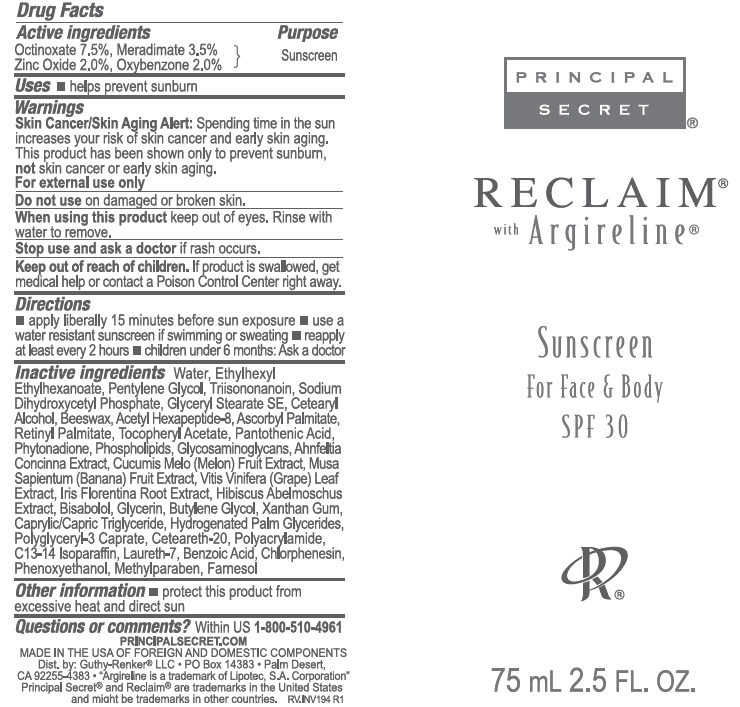 DRUG LABEL: Principal Secret Reclaim Sunscreen For Face and Body  SPF 30
NDC: 70605-014 | Form: CREAM
Manufacturer: Guthy-Renker LLC
Category: otc | Type: HUMAN OTC DRUG LABEL
Date: 20240110

ACTIVE INGREDIENTS: Meradimate 3.5 mg/100 mL; Octinoxate 7.5 mg/100 mL; Oxybenzone 2 mg/100 mL; Zinc Oxide 3 mg/100 mL
INACTIVE INGREDIENTS: Water; Ethylhexyl Ethylhexanoate; Pentylene Glycol; Triisononanoin; Sodium Dihydroxycetyl Phosphate; Glyceryl Stearate SE; Cetostearyl Alcohol; Yellow Wax; Ahnfeltiopsis Concinna; Acetyl Hexapeptide-8; Lecithin, Soybean; .ALPHA.-TOCOPHEROL ACETATE; VITAMIN A PALMITATE; MUSKMELON; BANANA; Ascorbyl Palmitate; Pantothenic Acid; VITIS VINIFERA LEAF; IRIS X GERMANICA NOTHOVAR. FLORENTINA ROOT; ABELMOSCHUS MOSCHATUS SEED; LEVOMENOL; Hydrogenated Palm Glycerides; POLYOXYL 20 CETOSTEARYL ETHER; POLYGLYCERYL-3 DISTEARATE; Phytonadione; Polyacrylamide (10000 MW); C13-14 Isoparaffin; Laureth-7; Xanthan Gum; MEDIUM-CHAIN TRIGLYCERIDES; Butylene Glycol; Phenoxyethanol; Methylparaben; Chlorphenesin; Benzoic Acid

Principal Secret® Reclaim® Sunscreen For Face & Body SPF 30

Drug Fact Label

Active ingredient

Octinoxate 7.5%
Meradimate 3.5%
Zinc Oxide 2.0%
Oxybenzone 2.0%

Purpose

Sunscreen

Uses

- helps prevent sunburn

Warnings

Skin Cancer/Skin Aging Alert

Spending time in the sun increases your risk of skin cancer and early skin aging. This product has been shown only to prevent sunburn, not skin cancer or early skin aging.

For external use only.

Do not use

on damaged or broken skin.

When using this product keep out of eyes. Rinse with water to remove.

Stop use and ask a doctor if rash occurs

Keep out of reach of children.

If product is swallowed, get medical help or contact a Poison Control Center right away.

Directions

- apply liberally 15 minutes before sub exposure
- use a water resistant sunscreen if swimming or sweating
- reapply at least every 2 hours
- children under 6 months Ask a doctor.

Inactive ingredients

Water, Ethylhexyl Ethylhexanoate, Pentylene Glycol, Triisononanoin, Sodium Dihydroxycetyl Phosphate, Glyceryl Stearate SE, Cetearyl Alcohol, Beeswax, Glycosaminoglycans, Ahnfeltiopsis Concinna Extract, Acetyl Hexapeptide-8, Phospholipids, Tocopheryl Acetate, Retinyl Palmitate, Cucumis Melo (Melon) Fruit Extract, Musa Sapientum (Banana) Fruit Extract, Ascorbyl Palmitate, Pantothenic Acid, Vitis Vinifera (Grape) Leaf Extract, Iris Florentina Root Extract, Hibiscus Abelmoschus Extract, Bisabolol, Hydrogenated Palm Glycerides, Ceteareth-20, Polyglyceryl-3 Caprate, Phytonadione, Polyacrylamide, C13-14 Isoparaffin, Laureth-7, Xanthan Gum, Caprylic/Capric Triglyceride, Butylene Glycol, Phenoxyethanol, Methylparaben, Chlorphenesin, Benzoic Acid

Other Information

- protect this product from excessive heat and direct sun

Questions or comments?

800-510-4961

Dist. by: Guthy-Renker® LLC • PO Box 14383 • Palm Desert,
CA 92255-4383

PRINCIPAL DISPLAY PANEL - 75 mL Tube Label

PRINCIPAL
SECRET®

RECLAIM®
with Argireline®

Sunscreen
For Face & Body
SPF 30

75 mL 2.5 FL. OZ.